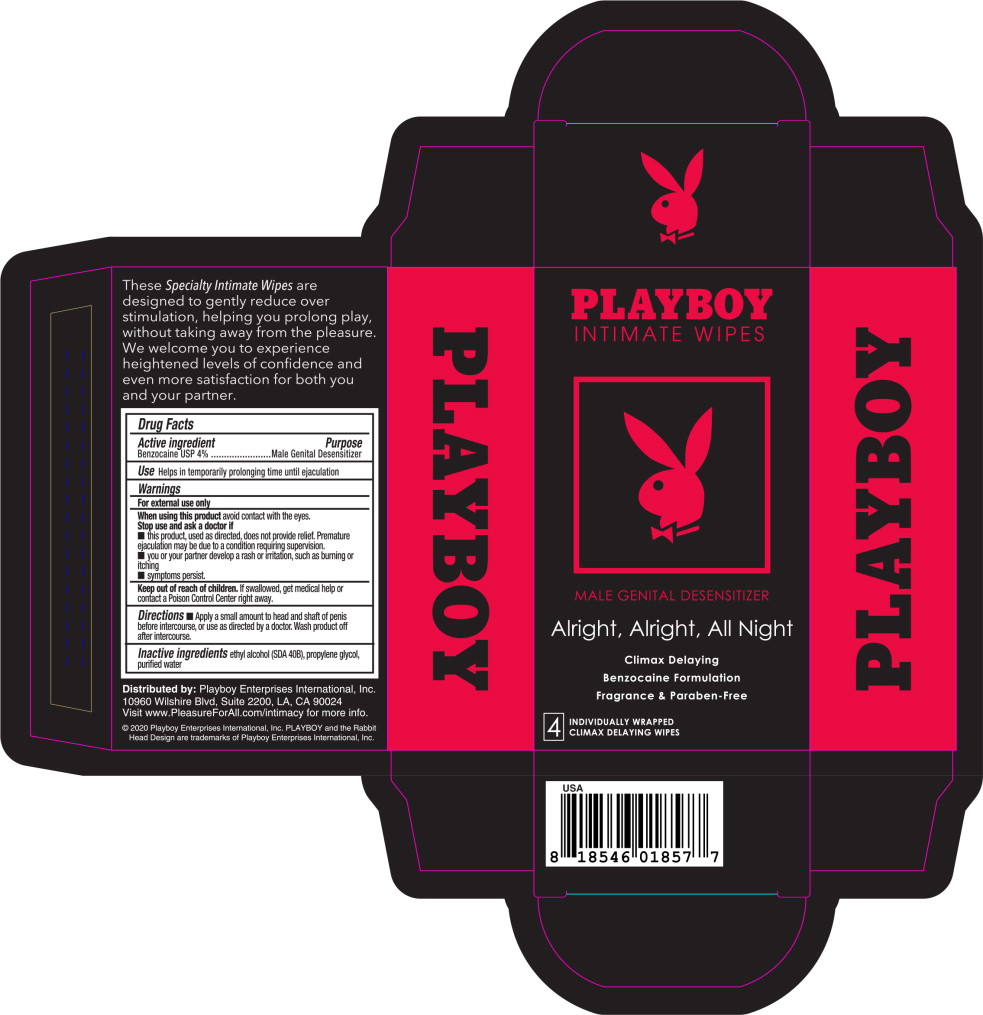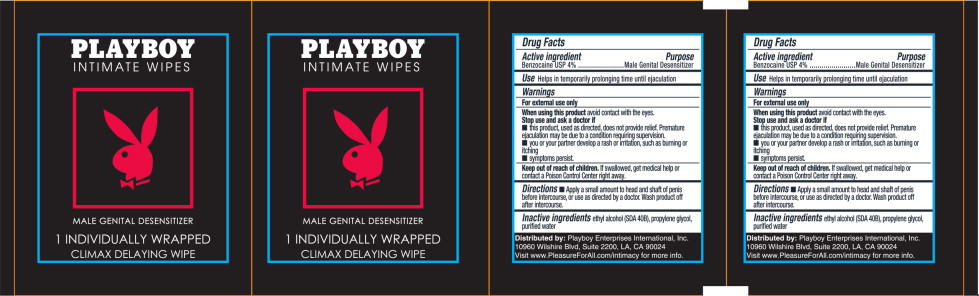 DRUG LABEL: Intimate Wipe
NDC: 69681-434 | Form: LIQUID
Manufacturer: Veru Inc.
Category: otc | Type: HUMAN OTC DRUG LABEL
Date: 20200608

ACTIVE INGREDIENTS: benzocaine 4 g/100 mL
INACTIVE INGREDIENTS: alcohol; water; propylene glycol

Drug Facts

Active ingredient

Benzocaine USP 4%

Purpose

Male Genital Desensitizer

Use

Helps in temporarily prolonging time until ejaculation

Warnings

For external use only

When using this product avoid contact with the eyes.

Stop use and ask a doctor if

- this product, used as directed, does not provide relief. Premature ejaculation may be due to a condition requiring supervision.
- You or your partner develop a rash or irritation, such as burning or itching
- Symptoms persist.

Keep out of reach of children.

If swallowed, get medical help or contact a Poison Control Center right away.

Directions

Apply a small amount to head and shaft of penis before intercourse, or use as directed by a doctor. Wash product off after intercourse.

Inactive ingredients

ethyl alcohol (SDA 40B), propylene glycol, purified water

Principal Display Panel – Box Label

PLAYBOY

INTIMATE WIPES

MALE GENITAL DESENSITIZER

Alright, Alright, All Night

Climax Delaying

Benzocaine Formulation

Fragrance & Paraben-Free

4 INDIVIDUALLY WRAPPED
CLIMAX DELAYING WIPES

Principal Display Panel – Packet Label

PLAYBOY

INTIMATE WIPES

MALE GENITAL DESENSITIZER

1 INDIVIDUALLY WRAPPED

CLIMAX DELAYING WIPE